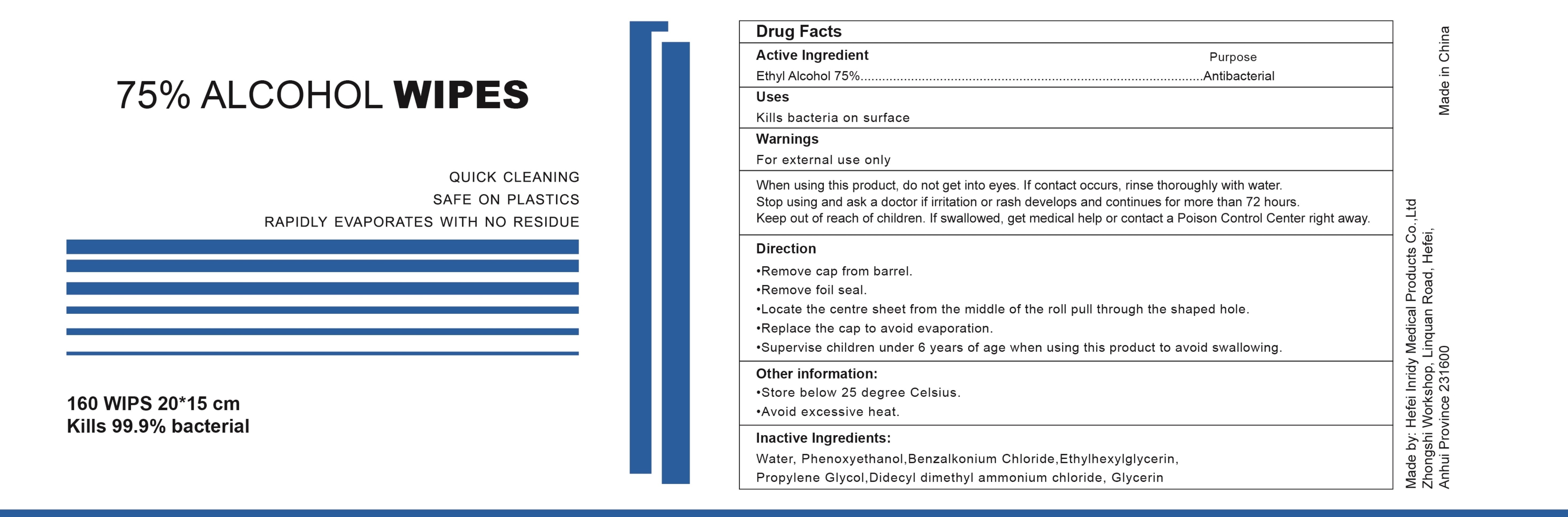 DRUG LABEL: ALCOHOL WIPES
NDC: 79683-003 | Form: CLOTH
Manufacturer: Hefei Inridy Medical Products Co., Ltd
Category: otc | Type: HUMAN OTC DRUG LABEL
Date: 20200717

ACTIVE INGREDIENTS: ALCOHOL 75 1/100 1
INACTIVE INGREDIENTS: ETHYLHEXYLGLYCERIN; PROPYLENE GLYCOL; GLYCERIN; PHENOXYETHANOL; WATER; BENZALKONIUM CHLORIDE; DIDECYLDIMONIUM CHLORIDE

ALCOHOL WIPES

Active Ingredient(s)

Ethyl Alcohol 75%

Purpose

Antibacterial

Use

Kills bacteria on surfac

Warnings

For external use only

Do not use

/

When using this product, do not get into eyes. If contact occurs, rinse thoroughly with water

STOP USE

Stop using and ask a doctor if irritation or rash develops and continues for more than 72 hours

Keep out of reach of children. If swallowed, get medical help or contact a Poison Control Center right away

Directions

Remove cap from barrel.
Remove foil seal.
Locate the centre sheet from the middle of the roll pull through the shaped hole.
Replace the cap to avoid evaporation
Supervise children under 6 years of age when using this product to avoid swallowing

Other information

Store below 25 degree Celsius.
Avoid excessive heat

Inactive ingredients

Water, Phenoxyethanol, Benzalkonium Chloride, Ethylhexylglycerin, Propylene Glycol, Didecyl dimethyl ammonium chloride, Glycerin